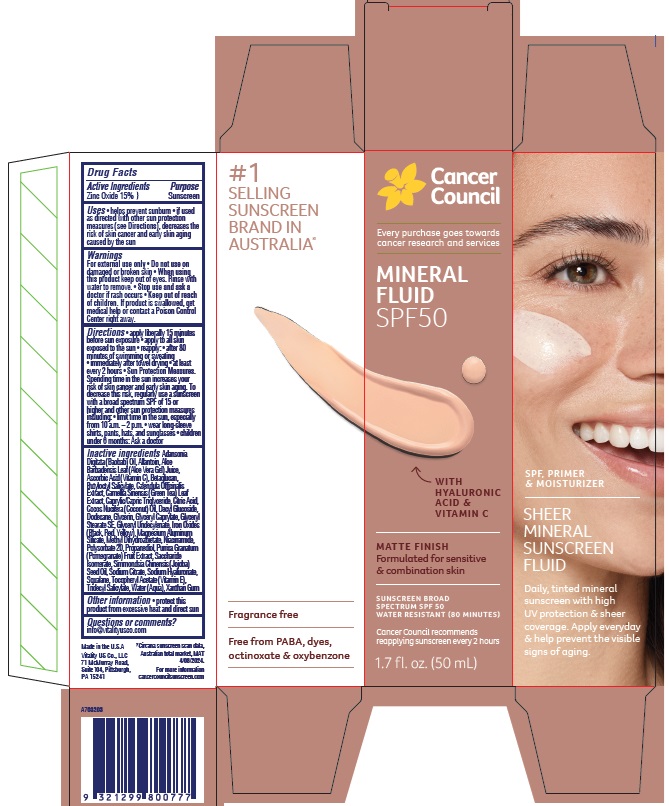 DRUG LABEL: Cancer Council Mineral Fluid SPF50
NDC: 84258-006 | Form: LOTION
Manufacturer: Vitality US Co.
Category: otc | Type: HUMAN OTC DRUG LABEL
Date: 20241024

ACTIVE INGREDIENTS: ZINC OXIDE 150 mg/1 mL
INACTIVE INGREDIENTS: DECYL GLUCOSIDE; GLYCERYL STEARATE SE; SACCHARIDE ISOMERATE; SQUALANE; YEAST .BETA.-D-GLUCAN; PROPANEDIOL; .ALPHA.-TOCOPHEROL ACETATE; ADANSONIA DIGITATA SEED OIL; ALLANTOIN; DODECANE; POMEGRANATE; SODIUM HYALURONATE; ASCORBIC ACID; ALOE VERA LEAF; BUTYLOCTYL SALICYLATE; WATER; GREEN TEA LEAF; CALENDULA OFFICINALIS FLOWER; MEDIUM-CHAIN TRIGLYCERIDES; COCONUT OIL; GLYCERYL CAPRYLATE; GLYCERYL 1-UNDECYLENATE; FERRIC OXIDE RED; FERROSOFERRIC OXIDE; FERRIC OXIDE YELLOW; MAGNESIUM ALUMINUM SILICATE; NIACINAMIDE; XANTHAN GUM; POLYSORBATE 20; JOJOBA OIL; CITRIC ACID MONOHYDRATE; TRIDECYL SALICYLATE; GLYCERIN; SODIUM CITRATE MONOHYDRATE

Cancer Council Mineral Fluid SPF50

Active Ingredients

Zinc Oxide 15%

Purpose

Sunscreen

Uses

- helps prevent sunburn
- if used as directed with other sun protection measures (see Directions), decreases the risk of skin cancer and early skin aging caused by the sun

Warnings

For external use only

Do not use

on damaged or broken skin

When using this product

keep out of eyes. Rinse with water to remove.

Stop use and ask a doctor

if rash occurs

Keep out of reach of children.

If product is swallowed, get medical help or contact a Poison Control Center right away.

Directions

- apply liberally 15 minutes before sun exposure
- apply to all skin exposed to the sun
- reapply:
- after 80 minutes of swimming or sweating
- immediately after towel drying
- at least every 2 hours
- Sun Protection Measures. Spending time in the sun increases your risk of skin cancer and early skin aging. To decrease this risk, regularly use a sunscreen with a broad spectrum SPF of 15 or higher and other sun protection measures including:
- limit time in the sun, especially from 10 a.m. - 2 p.m.
- wear long-sleeve shirts, pants, hats, and sunglasses
- children under 6 months: Ask a doctor

Inactive ingredients

Adansonia Digitata (Baobab) Oil, Allantoin, Aloe Barbadensis Leaf (Aloe Vera Gel) Juice, Ascorbic Acid (Vitamin C), Betaglucan, Butyloctyl Salicylate, Calendula Officinalis Extract, Camellia Sinensis (Green Tea) Leaf Extract, Caprylic/Capric Triglyceride, Citric Acid, Cocos Nucifera (Coconut) Oil, Decyl Glucoside, Dodecane, Glycerin, Glyceryl Caprylate, Glyceryl Stearate SE, Glyceryl Undecylenate, Iron Oxides (Black, Red, Yellow), Magnesium Aluminum Silicate, Methyl Dihydroabietate, Niacinamide, Polysorbate 20, Propanediol, Punica Granatum (Pomegranate) Fruit Extract, Saccharide Isomerate, Simmondsia Chinensis (Jojoba) Seed Oil, Sodium Citrate, Sodium Hyaluronate, Squalane, Tocopheryl Acetate (Vitamin E), Tridecyl Salicylate, Water (Aqua), Xanthan Gum

Other information

- protect this product from excessive heat and direct sun

Questions or comments?

info@vitalityusco.com